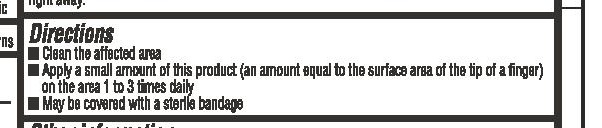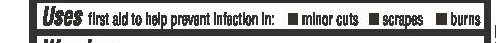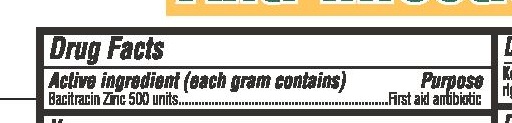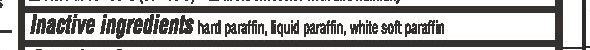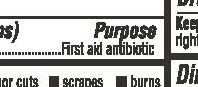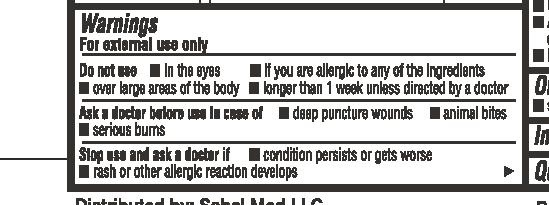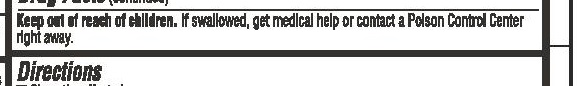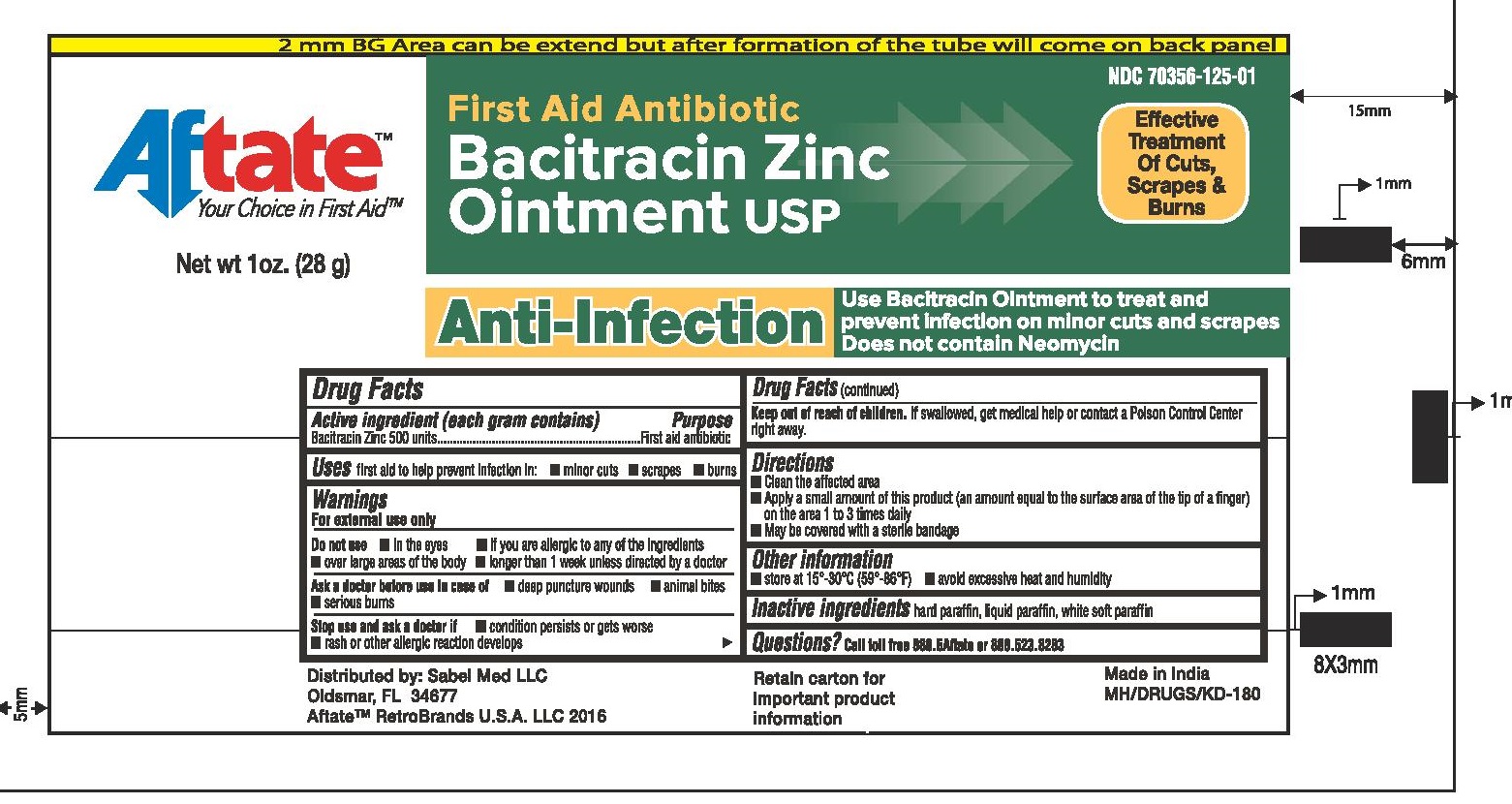 DRUG LABEL: Aftate Bacitracin Zinc
NDC: 70356-125 | Form: OINTMENT
Manufacturer: Sabel Med LLC
Category: otc | Type: HUMAN OTC DRUG LABEL
Date: 20160331

ACTIVE INGREDIENTS: BACITRACIN ZINC 500 [iU]/1 g
INACTIVE INGREDIENTS: PETROLATUM; LIGHT MINERAL OIL; MINERAL OIL

Bacitracin Zinc Ointment 1 oz (28g) tube
Bacitracin Zinc Ointment 0.5 oz (14g) tube